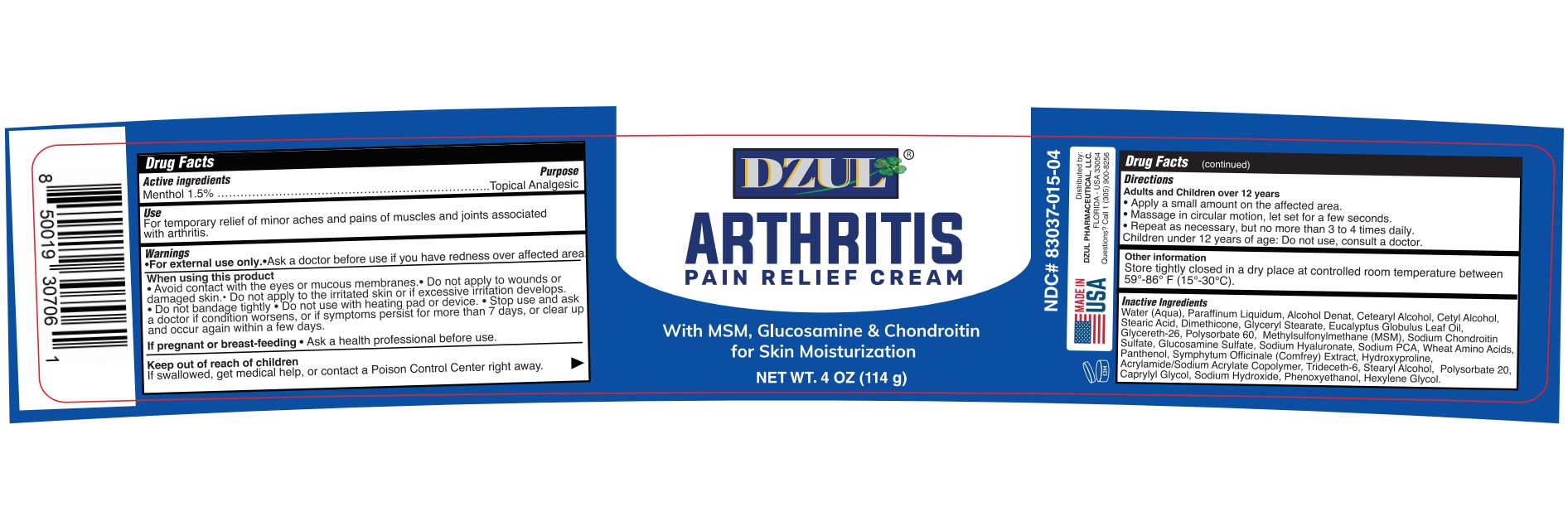 DRUG LABEL: DZUL ARTHRITIS PAIN RELIEF
NDC: 83037-015 | Form: CREAM
Manufacturer: Caball Sales, Inc.
Category: otc | Type: HUMAN OTC DRUG LABEL
Date: 20240408

ACTIVE INGREDIENTS: MENTHOL, UNSPECIFIED FORM 1.5 g/100 g
INACTIVE INGREDIENTS: EUCALYPTUS OIL; POLYSORBATE 60; DIMETHYL SULFONE; MINERAL OIL; GLYCERYL STEARATE SE; ACRYLIC ACID/SODIUM ACRYLATE COPOLYMER (1:1; 600 MPA.S AT 0.2%); AMINO ACIDS, WHEAT; PANTHENOL; ALCOHOL; STEARIC ACID; CETOSTEARYL ALCOHOL; CETYL ALCOHOL; DIMETHICONE; GLYCERETH-26; SODIUM CHONDROITIN SULFATE (PORCINE; 5500 MW); GLUCOSAMINE SULFATE; CAPRYLYL GLYCOL; SODIUM HYDROXIDE; SYMPHYTUM OFFICINALE WHOLE; HYDROXYPROLINE; STEARYL ALCOHOL; TRIDECETH-6; HYALURONATE SODIUM; SODIUM PYRROLIDONE CARBOXYLATE; PHENOXYETHANOL; HEXYLENE GLYCOL; POLYSORBATE 20; WATER

83037-015-04

ACTIVE INGREDIENT

Menthol 1.5%

PURPOSE

Topical Analgesic

USE

For the temporary relief of minor aches and pains of muscles and joints associated arthritis

WARNINGS

•For external use only.

•Ask a doctor before use if you have redness over affected area.

WHEN USING

Avoid contact with the eyes or mucous membranes.
Do not apply to wounds or damaged skin.
Do not apply to the irritated skin or if excessive irritation develops.
Do not bandage tightly.
Do not use with heating pad or device.

Stop use and ask a doctor if condition worsens, or if symptoms persist for more than 7 days, or clear up and occur again within a few days.

If pregnant or breast – feeding

Ask a health professional before use.

KEEP OUT OF REACH OF CHILDREN

If swallowed, get medical help, or contact a Poison Control Center right away.

DIRECTIONS

Adults and Children over 12 years

Apply a small amount on the affected area.
Massage in circular motion, let set for a few seconds.
Repeat as necessary, but no more than 3 to 4 times daily.

Children under 12 years of age: Do not use, consult a doctor.

OTHER INFORMATION

Store tightly closed in a dry place at controlled room temperature between 59-86 F (15°-30° C).

INACTIVE INGREDIENT

Water (Aqua), Paraffinum Liquidum, Alcohol Denat, Cetearyl Alcohol, Cetyl Alcohol, Stearic Acid, Dimethicone, Glyceryl Stearate, Eucalyptus Globulus Leaf Oil, Glycereth-26, Polysorbate 60, Methylsulfonylmethane (MSM), Sodium Chondroitin Sulfate, Glucosamine Sulfate, Sodium Hyaluronate, Sodium PCA, Wheat Amino Acids, Panthenol, Symphytum Officinale (Comfrey) Extract, Hydroxyproline, Acrylamide/Sodium Acrylate Copolymer, Trideceth-6, Stearyl Alcohol, Polysorbate 20, Caprylyl Glycol, Sodium Hydroxide, Phenoxyethanol, Hexylene Glycol.